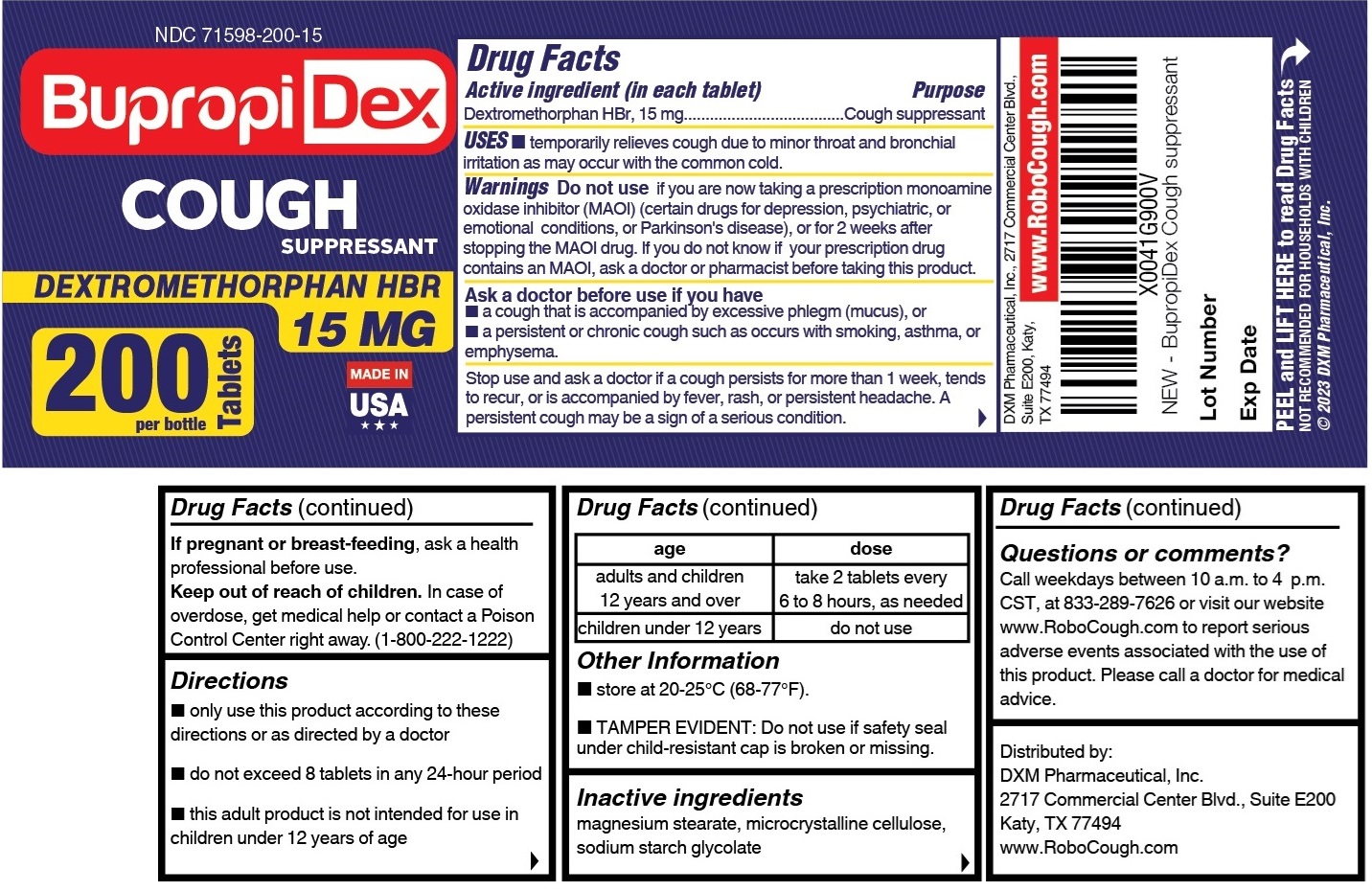 DRUG LABEL: BupropiDex
NDC: 71598-200 | Form: TABLET
Manufacturer: DXM Pharmacuetical, Inc.
Category: otc | Type: HUMAN OTC DRUG LABEL
Date: 20251006

ACTIVE INGREDIENTS: DEXTROMETHORPHAN HYDROBROMIDE 15 mg/1 1
INACTIVE INGREDIENTS: MAGNESIUM STEARATE; MICROCRYSTALLINE CELLULOSE; SODIUM STARCH GLYCOLATE TYPE A

Active ingredient

(in each tablet) Dextromethrophan HBr 15 mg

Purpose

Cough suppressant

Uses

Temporarily relieves cough due to minor throat and bronchial irritation as may occur with the common cold.

Warning

Do not useif you are now taking a prescription monoamine oxidase inhibitor (MAOI) (certain drugs for depression, psychiatric, or emotional conditions, or Parkinson's disease), or for 2 weeks after stopping the MAOI drug. If you do not know if your prescription drug contains an MAOI, ask a doctor or pharmacist before taking this product.

Ask a doctor before use ifyou have
• a cough that is accompanied by excessive phlegm (mucus), or
• a persistent or chronic cough such as occurs with smoking, asthma, or emphysema.

Stop use and ask a doctor ifa cough persists for more than 1 week, tends to recur, or is accompanied by fever, rash, or persistent headache. A persistent cough may be a sign of a serious condition.

If pregnant or breast-feeding, ask a health professional before use.

Keep out of reach of children. In case of overdose, get medical help or contact a Poison Control Center right away. (1-800-222-1222)

Directions

- only use this product according to these directions or as directed by a doctor
- do not exceed 8 tablets in any 24-hour period.
- this adult product is not intended for use in children under 12 years of age.

age | dose
adults and children 12 years and over | take 2 tablets every 6 to 8 hours, as needed
children under 12 years | do not use

Other information

• store at 20-25°C (68-77°F). Do not refrigerate.
• TAMPER EVIDENT: Do not use if safety seal under child-resistant cap is broken or missing.

Inactive ingredients

magnesium stearate, microcrystalline cellulose, sodium starch glycolate

Questions or comments?

Call weekdays between 10 a.m. to 4 p.m. CST, at 833-289-7626 or visit our website www.RoboCough.com to report serious adverse events associated with the use of this product. Please call a doctor for medical advice.

Distributed by:
DXM Pharmaceutical, Inc. 2717 Commercial Center Blvd., Suite E200
Katy, TX 77 494

Copyright 2023. Patent Pending. www.RoboCough.com.